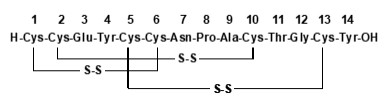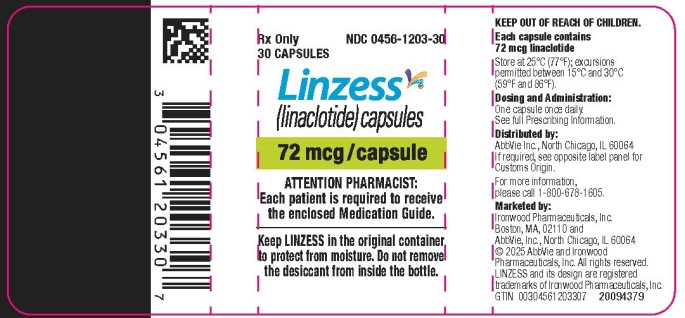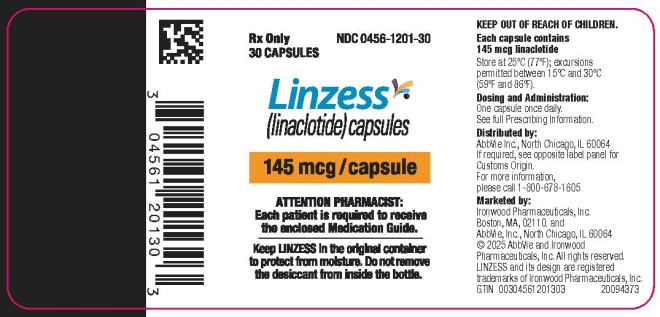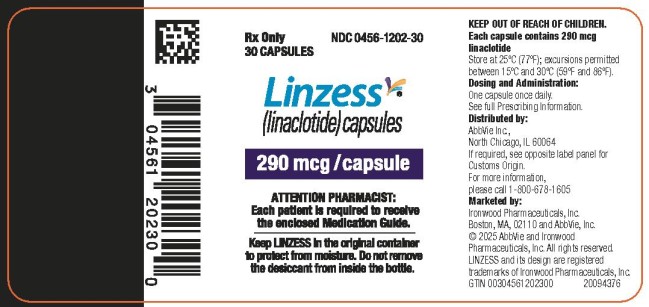 DRUG LABEL: Linzess
NDC: 0456-1201 | Form: CAPSULE, GELATIN COATED
Manufacturer: Allergan, Inc.
Category: prescription | Type: HUMAN PRESCRIPTION DRUG LABEL
Date: 20251104

ACTIVE INGREDIENTS: LINACLOTIDE 145 ug/1 1
INACTIVE INGREDIENTS: CALCIUM CHLORIDE; LEUCINE; CELLULOSE, MICROCRYSTALLINE; TITANIUM DIOXIDE; HYPROMELLOSE, UNSPECIFIED; GELATIN, UNSPECIFIED

HIGHLIGHTS OF PRESCRIBING INFORMATION

These highlights do not include all the information needed to use LINZESS safely and effectively. See full prescribing information for LINZESS.
LINZESS® (linaclotide) capsules, for oral use
Initial U.S. Approval: 2012

RECENT MAJOR CHANGES

Indications and Usage (1) | 11/2025
Dosage and Administration, Recommended Dosage (2.1) | 11/2025
Warnings and Precautions, Diarrhea (5.2) | 11/2025

WARNING: RISK OF SERIOUS DEHYDRATION IN PEDIATRIC PATIENTS LESS THAN 2 YEARS OF AGE

See full prescribing information for complete boxed warning.

- LINZESS is contraindicated in patients less than 2 years of age; in neonatal mice, linaclotide caused deaths due to dehydration. (4, 5.1, 8.4)

1 INDICATIONS AND USAGE

LINZESS is a guanylate cyclase-C agonist indicated for treatment of:

- Irritable bowel syndrome with constipation (IBS-C) in adults and pediatric patients 7 years of age and older. (1)
- Chronic idiopathic constipation (CIC) in adults. (1)
- Functional constipation (FC) in pediatric patients 6 years of age and older. (1)

2 DOSAGE AND ADMINISTRATION

The recommended dosage in adults is:

- IBS-C: 290 mcg orally once daily. (2.1)
- CIC: 145 mcg orally once daily or 72 mcg orally once daily based on individual presentation or tolerability. (2.1)

The recommended dosage in pediatric patients:

- 7 years of age and older with IBS-C: 145 mcg orally once daily. (2.1)
- 6 years of age and older with FC: 72 mcg orally once daily. (2.1)

Administration Instructions (2.2):

- Take on empty stomach at least 30 minutes prior to a meal at approximately the same time each day.
- Do not crush or chew LINZESS capsule or capsule contents.
- For patients who have difficulty swallowing capsules whole or those with a nasogastric or gastrostomy tube, see full prescribing information for instructions for opening the capsule and administering with applesauce or water.

3 DOSAGE FORMS AND STRENGTHS

Capsules: 72 mcg, 145 mcg and 290 mcg (3)

4 CONTRAINDICATIONS

- Patients less than 2 years of age. (4, 5.1, 8.4)
- Patients with known or suspected mechanical gastrointestinal obstruction. (4)

5 WARNINGS AND PRECAUTIONS

Diarrhea: Patients may experience severe diarrhea. If severe diarrhea occurs, suspend dosing and rehydrate the patient. (5.2)

6 ADVERSE REACTIONS

- Most common adverse reactions (≥2%) reported in adult patients with IBS-C or CIC are: diarrhea, abdominal pain, flatulence and abdominal distension. (6.1)
- Most common adverse reaction (≥2%) reported in pediatric patients with FC or IBS-C is diarrhea. (6.1)

To report SUSPECTED ADVERSE REACTIONS, contact AbbVie, Inc. at 1-800-678-1605 or FDA at 1-800-FDA-1088 or www.fda.gov/medwatch.

FULL PRESCRIBING INFORMATION

WARNING: RISK OF SERIOUS DEHYDRATION IN PEDIATRIC PATIENTS LESS THAN 2 YEARS OF AGE

LINZESS is contraindicated in patients less than 2 years of age; in nonclinical studies in neonatal mice, administration of a single, clinically relevant adult oral dose of linaclotide caused deaths due to dehydration [see Contraindications (4), Warnings and Precautions (5.1), Use in Specific Populations (8.4)].

1 INDICATIONS AND USAGE

LINZESS is indicated for the treatment of:

• irritable bowel syndrome with constipation (IBS-C) in adults and pediatric patients 7 years of age and older

• chronic idiopathic constipation (CIC) in adults

• functional constipation (FC) in pediatric patients 6 years of age and older

2 DOSAGE AND ADMINISTRATION

2.1 Recommended Dosage

Irritable Bowel Syndrome with Constipation (IBS-C):

The recommended dosage of LINZESS is:

• Adults: 290 mcg orally once daily

• Pediatric patients 7 years of age and older: 145 mcg orally once daily

Chronic Idiopathic Constipation (CIC) in Adults

The recommended dosage of LINZESS in adults is 145 mcg orally once daily. A dosage of 72 mcg once daily may be used based on individual presentation or tolerability.

Functional Constipation (FC) in Pediatric Patients 6 Years of Age and Older

The recommended dosage of LINZESS in pediatric patients 6 years of age and older is 72 mcg orally once daily.

2.2 Preparation and Administration Instructions

• Take LINZESS on an empty stomach, at least 30 minutes prior to a meal, at approximately the same time each day.

• If a dose is missed, skip the missed dose and take the next dose at the regular time. Do not take 2 doses at the same time.

• Do not crush or chew LINZESS capsule or capsule contents.

• Swallow LINZESS capsule whole.

• For patients who are unable to swallow the capsule whole, LINZESS capsules can be opened and administered orally in either applesauce or with water or administered with water via a nasogastric or gastrostomy tube. Sprinkling of LINZESS beads on other soft foods or in other liquids has not been tested.

Oral Administration in Applesauce:

1. Place one teaspoonful of room-temperature applesauce into a clean container.
2. Open the capsule.
3. Sprinkle the entire contents (beads) on applesauce.
4. Consume the entire contents immediately. Do not chew the beads. Do not store the bead-applesauce mixture for later use.

Oral Administration in Water:

1. Pour approximately 30 mL of room-temperature bottled water into a clean cup.
2. Open the capsule.
3. Sprinkle the entire contents (beads) into the water.
4. Gently swirl beads and water for at least 20 seconds.
5. Swallow the entire mixture of beads and water immediately.
6. Add another 30 mL of water to any beads remaining in cup, swirl for 20 seconds, and swallow immediately.
7. Do not store the bead-water mixture for later use.

Note: The drug is coated on the surface of the beads and will dissolve off the beads into the water. The beads will remain visible and will not dissolve. Therefore, it is not necessary to consume all the beads to deliver the complete dose.

Administration with Water via a Nasogastric or Gastrostomy Tube:

1. Open the capsule and empty the beads into a clean container with 30 mL of room-temperature bottled water.
2. Mix by gently swirling beads for at least 20 seconds.
3. Draw-up the beads and water mixture into an appropriately sized catheter-tipped syringe and apply rapid and steady pressure (10 mL/10 seconds) to dispense the syringe contents into the tube.
4. Add another 30 mL of water to any beads remaining in the container and repeat the process.
5. After administering the bead-water mixture, flush nasogastric/ gastrostomy tube with a minimum of 10 mL of water.

Note: It is not necessary to flush all the beads through to deliver the complete dose.

3 DOSAGE FORMS AND STRENGTHS

LINZESS capsules are white to off-white opaque:

- 72 mcg; gray imprint “FL 72”
- 145 mcg; gray imprint “FL 145”
- 290 mcg; gray imprint “FL 290”

4 CONTRAINDICATIONS

LINZESS is contraindicated in:

- Patients less than 2 years of age due to the risk of serious dehydration [see Warnings and Precautions (5.1), Use in Specific Populations (8.4)].
- Patients with known or suspected mechanical gastrointestinal obstruction.

5 WARNINGS AND PRECAUTIONS

5.1 Risk of Serious Dehydration in Pediatric Patients Less Than 2 Years of Age

LINZESS is contraindicated in patients less than 2 years of age. In neonatal mice (human age equivalent of approximately 0 to 28 days), linaclotide increased fluid secretion as a consequence of age-dependent elevated GC-C agonism which was associated with increased mortality within the first 24 hours due to dehydration. There was no age-dependent trend in GC-C intestinal expression in a clinical study of children 2 to less than 18 years of age; however, there are insufficient data available on GC-C intestinal expression in children less than 2 years of age to assess the risk of developing diarrhea and its potentially serious consequences in these patients [see Warnings and Precautions (5.2) and Use in Specific Populations (8.4)].

5.2 Diarrhea

In adults, diarrhea was the most common adverse reaction of LINZESS-treated patients in the pooled IBS-C and CIC double-blind placebo-controlled trials. The incidence of diarrhea was similar between the IBS-C and CIC populations. Severe diarrhea was reported in 2% of adult patients with IBS-C or CIC treated with LINZESS 145 mcg or 290 mcg once daily, and in <1% of adult patients with CIC treated with LINZESS 72 mcg once daily [see Adverse Reactions (6.1)].

In pediatric patients, diarrhea was also the most common adverse reaction of LINZESS-treated patients in IBS-C and FC clinical trials. In two double-blind trials, diarrhea was reported in 4% of pediatric patients 6 to 17 years of age with FC treated with LINZESS 72 mcg once daily, and 7% and 8% of pediatric patients 7 to 17 years of age with IBS-C treated with LINZESS 145 mcg and 290 mcg once daily, respectively. In clinical trials, severe diarrhea was reported in one pediatric patient with FC treated with LINZESS 72 mcg once daily [see Adverse Reactions (6.1)] and in one pediatric patient with IBS-C treated with LINZESS at a dosage higher than the recommended 145 mcg once daily dosage for IBS-C.

In post-marketing experience, severe diarrhea associated with dizziness, syncope, hypotension and electrolyte abnormalities (hypokalemia and hyponatremia) requiring hospitalization or intravenous fluid administration have been reported in patients treated with LINZESS.

If severe diarrhea occurs, suspend dosing and rehydrate the patient.

6 ADVERSE REACTIONS

6.1 Clinical Trials Experience

Because clinical trials are conducted under widely varying conditions, adverse reaction rates observed in the clinical trials of a drug cannot be directly compared with rates in the clinical trials of another drug and may not reflect the rates observed in practice.

Demographic characteristics were comparable between treatment groups in all studies [see Clinical Studies (14.1, 14.2, 14.3, 14.4)].

Irritable Bowel Syndrome with Constipation (IBS-C) in Adults

Most Common Adverse Reactions

The data described below reflect exposure to LINZESS in the two placebo-controlled clinical trials involving 1605 adult patients with IBS-C (Trials 1 and 2) [see Clinical Studies (14.1)]. Patients were randomized to receive placebo or 290 mcg LINZESS once daily on an empty stomach for up to 26 weeks. Table 1 provides the incidence of adverse reactions reported in at least 2% of IBS-C patients in the LINZESS treatment group and at an incidence that was greater than in the placebo group.

Table 1: Most Common Adverse Reactionsa in Two Placebo-Controlled Trials (1 and 2) in Adult Patients with IBS-C
Adverse Reactions | LINZESS 290 mcg [N=807] % | Placebo [N=798] %
Gastrointestinal Diarrhea Abdominal painb Flatulence Abdominal distension | 20 7 4 2 | 3 5 2 1
Infections and Infestations Viral Gastroenteritis | 3 | 1
Nervous System Disorders Headache | 4 | 3

a: Reported in at least 2% of LINZESS-treated patients and at an incidence greater than placebo

b: “Abdominal pain” term includes abdominal pain, upper abdominal pain, and lower abdominal pain.

Adverse reactions in an additional placebo-controlled trial in 614 IBS-C patients randomized to placebo or LINZESS 290 mcg once daily on an empty stomach for 12 weeks (Trial 6) were similar to those in Table 1.

Diarrhea

Diarrhea was the most commonly reported adverse reaction of the LINZESS-treated patients in the pooled IBS-C pivotal placebo-controlled trials. In these trials, 20% of LINZESS-treated patients reported diarrhea compared to 3% of placebo-treated patients. Severe diarrhea was reported in 2% of the LINZESS-treated patients versus less than 1% of the placebo-treated patients, and 5% of LINZESS-treated patients discontinued due to diarrhea vs less than 1% of placebo-treated patients. The majority of reported cases of diarrhea started within the first 2 weeks of LINZESS treatment [see Warnings and Precautions (5.2)].

Adverse Reactions Leading to Discontinuation

In placebo-controlled trials in patients with IBS-C, 9% of patients treated with LINZESS and 3% of patients treated with placebo discontinued prematurely due to adverse reactions. In the LINZESS-treatment group, the most common reasons for discontinuation due to adverse reactions were diarrhea (5%) and abdominal pain (1%). In comparison, less than 1% of patients in the placebo group withdrew due to diarrhea or abdominal pain.

Adverse Reactions Leading to Dose Reductions

In the open-label, long-term trials, 2147 patients with IBS-C received 290 mcg of LINZESS daily for up to 18 months. In these trials, 29% of patients had their dose reduced or suspended secondary to adverse reactions, the majority of which were diarrhea or other GI adverse reactions.

Less Common Adverse Reactions

Defecation urgency, fecal incontinence, vomiting, and gastroesophageal reflux disease were reported in <2% of patients in the LINZESS-treatment group and at an incidence greater than in the placebo treatment group.

Chronic Idiopathic Constipation (CIC) in Adults

Most Common Adverse Reactions

The data described below reflect exposure to LINZESS in the two double-blind placebo-controlled clinical trials of 1275 adult patients with CIC (Trials 3 and 4) [see Clinical Studies (14.3)]. Patients were randomized to receive placebo or 145 mcg LINZESS or 290 mcg LINZESS once daily on an empty stomach, for at least 12 weeks. Table 2 provides the incidence of adverse reactions reported in at least 2% of CIC patients in the 145 mcg LINZESS treatment group and at an incidence that was greater than in the placebo treatment group.

Table 2: Most Common Adverse Reactionsa in the Two Placebo-controlled Trials (3 and 4) in Adult Patients with CIC
Adverse Reactions | LINZESS 145 mcg [N=430] % | Placebo [N=423] %
Gastrointestinal Diarrhea Abdominal painb Flatulence Abdominal distension | 16 7 6 3 | 5 6 5 2
Infections and Infestations Upper respiratory tract infection Sinusitis | 5 3 | 4 2

a: Reported in at least 2% of LINZESS-treated patients and at an incidence greater than placebo

b: “Abdominal pain” term includes abdominal pain, upper abdominal pain, and lower abdominal pain.

The safety of a 72 mcg dose was evaluated in an additional placebo-controlled trial in which 1223 patients were randomized to LINZESS 72 mcg, 145 mcg, or placebo once daily for 12 weeks (Trial 5).

In Trial 5, adverse reactions that occurred at a frequency of ≥ 2% in LINZESS-treated patients (N=411 in each LINZESS 72 mcg and 145 mcg group) and at a higher rate than placebo (N=401) were:

- Diarrhea (LINZESS 72 mcg 19%; LINZESS 145 mcg 22%; placebo 7%)
- Abdominal distension (LINZESS 72 mcg 2%; LINZESS 145 mcg 1%; placebo < 1%)

Diarrhea

In Trials 3 and 4 (pooled) and Trial 5, diarrhea was the most commonly reported adverse reaction in LINZESS-treated patients in the CIC placebo-controlled studies.

In all trials, the majority of reported cases of diarrhea started within the first 2 weeks of LINZESS treatment.

Severe diarrhea was reported in less than 1% of the 72 mcg LINZESS-treated patients (Trial 5), in 2% of the 145 mcg LINZESS-treated patients (Trials 3, 4, and 5), and less than 1% of the placebo-treated patients (Trials 3, 4, and 5) [see Warnings and Precautions (5.2)].

Adverse Reactions Leading to Discontinuation

In placebo-controlled trials in patients with CIC, 3% of patients treated with 72 mcg (Trial 5) and between 5% and 8% (Trials 3, 4, and 5) of patients treated with 145 mcg of LINZESS discontinued prematurely due to adverse reactions compared to between less than 1% and 4% (Trials 3, 4, and 5) of patients treated with placebo.

In patients treated with 72 mcg LINZESS, the most common reason for discontinuation due to adverse reactions was diarrhea (2% in Trial 5) and, in patients treated with 145 mcg LINZESS, the most common reasons for discontinuation due to adverse reactions were diarrhea (between 3% and 5% in Trials 3, 4, and 5) and abdominal pain (1% in Trials 3 and 4). In comparison, less than 1% of patients in the placebo group withdrew due to diarrhea or abdominal pain (Trials 3, 4, and 5).

Adverse Reactions Leading to Dose Reductions

In the open-label, long-term trials, 1129 patients with CIC received 290 mcg of LINZESS daily for up to 18 months. In these trials, 27% of patients had their dose reduced or suspended secondary to adverse reactions, the majority of which were diarrhea or other GI adverse reactions.

Less Common Adverse Reactions

Defecation urgency, fecal incontinence, dyspepsia, and viral gastroenteritis were reported in less than 2% of patients in the LINZESS treatment group and at an incidence greater than in the placebo treatment group.

Functional Constipation (FC) in Pediatric Patients 6 Years of Age and Older

The safety of LINZESS 72 mcg once daily was evaluated in pediatric patients 6 to 17 years of age with FC in a 12-week double-blind, placebo-controlled clinical trial (Trial 7) [see Clinical Studies (14.4)]. There were 164 patients per treatment group.

Diarrhea was the most common adverse reaction and was reported in 4% of LINZESS-treated patients compared to 2% of placebo-treated patients. One patient in the LINZESS-treated group reported severe diarrhea and discontinued treatment. No patient in the placebo-treated group discontinued treatment due to severe diarrhea. Most reported cases of diarrhea started within the first 2 weeks of LINZESS treatment [see Warnings and Precautions (5.2)].

Other adverse reactions reported at a higher incidence in the LINZESS group than the placebo group included nausea (2 patients) and abdominal discomfort and dehydration (1 patient each).

IBS-C in Pediatric Patients 7 Years of Age and Older

The safety of LINZESS 145 mcg once daily was evaluated in 55 pediatric patients 7 to 17 years of age with IBS-C in a 12-week double-blind, parallel-group clinical trial (Trial 8) [see Clinical Studies (14.2)].

The safety profile in pediatric patients treated with LINZESS was similar to the safety profile from trials in adults with IBS-C and CIC and in pediatric patients with FC. Diarrhea was the most common adverse reaction reported in 7% of 145 mcg LINZESS-treated pediatric patients. Most reported cases of diarrhea started within the first 2 weeks of LINZESS treatment [see Warnings and Precautions (5.2)].

6.2 Postmarketing Experience

The following adverse reactions have been identified during post approval use of LINZESS. Because these reactions are reported voluntarily from a population of uncertain size, it is not always possible to reliably estimate their frequency or establish a causal relationship to drug exposure.

Hypersensitivity reactions: Anaphylaxis, angioedema, rash (including hives or urticaria)

Gastrointestinal reactions: Hematochezia, nausea, rectal hemorrhage

8 USE IN SPECIFIC POPULATIONS

8.1 Pregnancy

Risk Summary

Linaclotide and its active metabolite are negligibly absorbed systemically following oral administration [see Clinical Pharmacology (12.3)], and maternal use is not expected to result in fetal exposure to the drug. The available data on LINZESS use in pregnant women are not sufficient to inform any drug-associated risk for major birth defects and miscarriage. In animal developmental studies, no effects on embryo-fetal development were observed with oral administration of linaclotide in rats and rabbits during organogenesis at doses much higher than the maximum recommended human dosage. Severe maternal toxicity associated with effects on fetal morphology were observed in mice (see Data).

The estimated background risk of major birth defects and miscarriage for the indicated population is unknown. All pregnancies have a background risk of birth defect, loss, or other adverse outcomes. In the United States general population, the estimated background risk of major birth defects and miscarriage in clinically recognized pregnancies is 2% to 4% and 15% to 20%, respectively.

Data

Animal Data

The potential for linaclotide to cause harm to embryo-fetal development was studied in rats, rabbits and mice. In pregnant mice, oral dose levels of at least 40,000 mcg/kg/day given during organogenesis produced severe maternal toxicity including death, reduction of gravid uterine and fetal weights, and effects on fetal morphology. Oral doses of 5,000 mcg/kg/day did not produce maternal toxicity or any adverse effects on embryo-fetal development in mice. Oral administration of up to 100,000 mcg/kg/day in rats and 40,000 mcg/kg/day in rabbits during organogenesis produced no maternal toxicity and no effects on embryo-fetal development. Additionally, oral administration of up to 100,000 mcg/kg/day in rats during organogenesis through lactation produced no developmental abnormalities or effects on growth, learning and memory, or fertility in the offspring through maturation.

The maximum recommended human dose is approximately 5 mcg/kg/day, based on a 60-kg body weight. Limited systemic exposure to linaclotide was achieved in animals during organogenesis (AUC = 40, 640, and 25 ng•hr/mL in rats, rabbits, and mice, respectively, at the highest dose levels). Linaclotide and its active metabolite are not measurable in human plasma following administration of the recommended clinical dosages. Therefore, animal and human doses should not be compared directly for evaluating relative exposure.

8.2 Lactation

Risk Summary

Linaclotide and its active metabolite were not detected in the milk of lactating women (see Data). In adults, concentrations of linaclotide and its active metabolite were below the limit of quantitation in plasma following multiple doses of LINZESS [see Clinical Pharmacology (12.3)]. Maternal use of LINZESS is not expected to result in exposure to linaclotide or its active metabolite in breastfed infants. There is no information on the effects of linaclotide or its active metabolite on milk production. The developmental and health benefits of breastfeeding should be considered along with the mother’s clinical need for LINZESS and any potential adverse effects on the breastfed infant from LINZESS or from the underlying maternal condition.

Data

Following oral administration of 72 mcg, 145 mcg, or 290 mcg of LINZESS once daily for 3 days to breastfeeding mothers taking linaclotide therapeutically, the concentrations of linaclotide and its metabolite were below the limits of quantitation (<0.25 ng/mL and <1 ng/mL, respectively) in all breast milk samples collected over 24 hours.

8.4 Pediatric Use

LINZESS is contraindicated in patients less than 2 years of age due to the risk of serious dehydration. In nonclinical studies, deaths occurred within 24 hours in neonatal mice (human age equivalent of approximately 0 to 28 days) following oral administration of linaclotide which increased fluid secretion as a consequence of age-dependent elevated GC-C agonism resulting in rapid and severe dehydration (see Juvenile Animal Toxicity Data).

In a clinical GC-C ontogeny study in children 6 months to less than 18 years of age (N=99) to measure GC-C mRNA expression levels in duodenal and colonic samples to evaluate the risk of diarrhea and severe dehydration due to GC-C agonism, there was insufficient data on GC-C intestinal expression to assess the risk of developing diarrhea and its potentially serious consequences in children less than 2 years of age [see Warnings and Precautions (5.1)].

Functional Constipation (FC)

The safety and effectiveness of LINZESS for the treatment of FC have been established in pediatric patients 6 years of age and older. Use of LINZESS for this indication is supported by evidence from adequate and well-controlled studies in adults and pediatric patients 6 to 17 years of age. The safety of LINZESS in adult and pediatric patients in these clinical studies was similar [see Adverse Reactions (6.1) and Clinical Studies (14.4)].

The safety and effectiveness of LINZESS for the treatment of FC have not been established in pediatric patients less than 6 years of age.

Irritable Bowel Syndrome with Constipation (IBS-C)

The safety and effectiveness of LINZESS for the treatment of IBS-C have been established in pediatric patients 7 years of age and older. Use of LINZESS for this indication is supported by evidence from adequate and well-controlled studies in adults and pediatric patients 7 to 17 years of age. The safety of LINZESS in adult and pediatric patients in these clinical studies was similar [see Adverse Reactions (6.1) and Clinical Studies (14.2)].

The safety and effectiveness of LINZESS for the treatment of IBS-C have not been established in pediatric patients less than 7 years of age.

Juvenile Animal Toxicity Data

In toxicology studies in neonatal mice, oral administration of linaclotide at 10 mcg/kg/day caused deaths on post-natal day 7 (human age equivalent of approximately 0 to 28 days). These deaths were due to rapid and severe dehydration produced by significant fluid shifts into the intestinal lumen resulting from GC-C agonism in neonatal mice [see Contraindications (4) and Warnings and Precautions (5.1)].

Tolerability to linaclotide increases with age in juvenile mice. In 2-week-old mice, linaclotide was well tolerated at a dose of 50 mcg/kg/day, but deaths occurred after a single oral dose of 100 mcg/kg. In 3-week-old mice, linaclotide was well tolerated at 100 mcg/kg/day, but deaths occurred after a single oral dose of 600 mcg/kg.

8.5 Geriatric Use

Irritable Bowel Syndrome with Constipation (IBS-C)
Of 2219 IBS-C patients in the placebo-controlled clinical studies of LINZESS (Trials 1, 2, and 6), 154 (7%) were 65 years of age and over, while 34 (2%) were 75 years and over. Clinical studies of LINZESS did not include sufficient numbers of patients aged 65 years and over to determine whether they respond differently from younger patients.

Chronic Idiopathic Constipation (CIC)
Of 2498 CIC patients in the placebo-controlled clinical studies of LINZESS (Trials 3, 4, and 5), 273 (11%) were 65 years of age and over, while 56 (2%) were 75 years and over. Clinical studies of LINZESS did not include sufficient numbers of patients aged 65 and over to determine whether they respond differently from younger patients. In general, dose selection for an elderly patient should be cautious reflecting the greater frequency of decreased hepatic, renal or cardiac function and of concomitant disease or other drug therapy.

10 OVERDOSAGE

Single LINZESS doses of 2897 mcg were administered to 22 healthy subjects; the safety profile in these subjects was consistent with that in the overall LINZESS-treated population, with diarrhea being the most commonly reported adverse reaction.

11 DESCRIPTION

LINZESS (linaclotide) is a guanylate cyclase-C (GC-C) agonist. Linaclotide is a 14-amino acid peptide with the following chemical name: L-cysteinyl-L-cysteinyl-L-glutamyl-L-tyrosyl-L-cysteinyl-L-cysteinyl-L-asparaginyl-L-prolyl-L-alanyl-L-cysteinyl-L-threonyl-glycyl-L-cysteinyl-L-tyrosine, cyclic (1-6), (2-10), (5-13)-tris (disulfide).

The molecular formula of linaclotide is C59H79N15O21S6 and its molecular weight is 1526.8. The amino acid sequence for linaclotide is shown below:

Linaclotide is an amorphous, white to off-white powder. It is slightly soluble in water and aqueous sodium chloride (0.9%). LINZESS contains linaclotide-coated beads in hard gelatin capsules. LINZESS is available as 72 mcg, 145 mcg and 290 mcg capsules for oral administration.

The inactive ingredients of LINZESS 72 mcg capsules include: calcium chloride dihydrate, L-histidine, microcrystalline cellulose, polyvinyl alcohol, and talc. The components of the capsule shell include gelatin and titanium dioxide.

The inactive ingredients of LINZESS 145 mcg and 290 mcg capsules include: calcium chloride dihydrate, hypromellose, L-leucine, and microcrystalline cellulose. The components of the capsule shell include gelatin and titanium dioxide.

12 CLINICAL PHARMACOLOGY

12.1 Mechanism of Action

Linaclotide is structurally related to human guanylin and uroguanylin and functions as a guanylate cyclase-C (GC-C) agonist. Both linaclotide and its active metabolite bind to GC-C and act locally on the luminal surface of the intestinal epithelium. Activation of GC-C results in an increase in both intracellular and extracellular concentrations of cyclic guanosine monophosphate (cGMP). Elevation in intracellular cGMP stimulates secretion of chloride and bicarbonate into the intestinal lumen, mainly through activation of the cystic fibrosis transmembrane conductance regulator (CFTR) ion channel, resulting in increased intestinal fluid and accelerated transit. In animal models, linaclotide has been shown to both accelerate GI transit and reduce intestinal pain.

In an animal model of visceral pain, linaclotide reduced abdominal muscle contraction and decreased the activity of pain-sensing nerves by increasing extracellular cGMP.

12.2 Pharmacodynamics

Food Effect

Taking LINZESS immediately after a high fat breakfast resulted in looser stools and a higher stool frequency compared with taking it in the fasted state [see Dosage and Administration (2.1, 2.2)]. In clinical trials, LINZESS was administered on an empty stomach, at least 30 minutes before a meal at approximately the same time each day.

12.3 Pharmacokinetics

Absorption

LINZESS is minimally absorbed with negligible systemic availability following oral administration. Concentrations of linaclotide and its active metabolite in plasma are below the limit of quantitation after oral doses of 72 mcg, 145 mcg, or 290 mcg were administered. Therefore, standard pharmacokinetic parameters such as area under the curve (AUC), maximum concentration (Cmax), and half-life (t½) cannot be calculated.

Food Effect

Neither linaclotide nor its active metabolite were detected in the plasma following administration of LINZESS 290 mcg once daily for 7 days both in the non-fed and fed state in healthy subjects.

Distribution

Given that linaclotide plasma concentrations following recommended oral doses are not measurable, linaclotide is not expected to be distributed to tissues to any clinically relevant extent.

Elimination

Metabolism

Linaclotide is metabolized within the gastrointestinal tract to its principal, active metabolite by loss of the terminal tyrosine moiety. Both linaclotide and the metabolite are proteolytically degraded within the intestinal lumen to smaller peptides and naturally occurring amino acids.

Excretion

Active peptide recovery in the stool samples of fed and fasted healthy subjects following administration of LINZESS 290 mcg once daily for seven days averaged about 5% (fasted) and about 3% (fed) and all of it as the active metabolite.

Specific Populations

Renal and Hepatic Impairment

Renal or hepatic impairment is not expected to affect the clearance of linaclotide or the active metabolite because linaclotide metabolism occurs within the gastrointestinal tract and plasma concentrations are not measurable in plasma following administration of the recommended dosage.

Drug Interaction Studies

No drug-drug interaction studies have been conducted with LINZESS. Systemic exposures of drug and active metabolite are negligible following oral administration.

Linaclotide does not interact with the cytochrome P450 enzyme system based on the results of in vitro studies. In addition, linaclotide does not interact with common efflux and uptake transporters (including the efflux transporter P-glycoprotein (P-gp)). Based on these in vitro data no drug-drug interactions through modulation of CYP enzymes or common transporters are anticipated.

13 NONCLINICAL TOXICOLOGY

13.1 Carcinogenesis, Mutagenesis, Impairment of Fertility

Carcinogenesis

In 2-year carcinogenicity studies, linaclotide was not tumorigenic in rats at doses up to 3500 mcg/kg/day or in mice at doses up to 6000 mcg/kg/day. The maximum recommended human dose is approximately 5 mcg/kg/day based on a 60-kg body weight. Limited systemic exposure to linaclotide and its active metabolite was achieved at the tested dose levels in animals, whereas no detectable exposure occurred in humans. Therefore, animal and human doses should not be compared directly for evaluating relative exposure.

Mutagenesis

Linaclotide was not genotoxic in an in vitro bacterial reverse mutation (Ames) assay or in the in vitro chromosomal aberration assay in cultured human peripheral blood lymphocytes.

Impairment of Fertility

Linaclotide had no effect on fertility or reproductive function in male and female rats at oral doses of up to 100,000 mcg/kg/day.

14 CLINICAL STUDIES

14.1 Irritable Bowel Syndrome with Constipation (IBS-C) in Adults

The efficacy of LINZESS for the treatment of IBS-C was established in two double-blind, placebo-controlled, randomized, multicenter trials in adult patients (Trials 1 (NCT00948818) and 2 (NCT00938717)). A total of 800 patients in Trial 1 and 804 patients in Trial 2 [overall mean age of 44 years (range 18 to 87 years), 90% female, 77% white, 19% black, and 12% Hispanic] received treatment with LINZESS 290 mcg or placebo once daily and were evaluated for efficacy. All patients met Rome II criteria for IBS and were required, during the 2-week baseline period, to meet the following criteria:

- a mean abdominal pain score of at least 3 on a 0-to-10-point numeric rating scale
- less than 3 complete spontaneous bowel movements (CSBMs) per week [a CSBM is a spontaneous bowel movement (SBM) that is associated with a sense of complete evacuation; a SBM is a bowel movement occurring in the absence of laxative use], and
- less than or equal to 5 SBMs per week.

The trial designs were identical through the first 12 weeks, and thereafter differed only in that Trial 1 included a 4-week randomized withdrawal (RW) period, and Trial 2 continued for 14 additional weeks (total of 26 weeks) of double-blind treatment. During the trials, patients were allowed to continue stable doses of bulk laxatives or stool softeners but were not allowed to take laxatives, bismuth, prokinetic agents, or other drugs to treat IBS-C or chronic constipation.

Efficacy of LINZESS was assessed using overall responder analyses and change-from-baseline endpoints. Results for endpoints were based on information provided daily by patients in diaries.

The 4 primary efficacy responder endpoints were based on a patient being a weekly responder for either at least 9 out of the first 12 weeks of treatment or at least 6 out of the first 12 weeks of treatment. For the 9 out of 12 weeks combined primary responder endpoint, a patient had to have at least a 30% reduction from baseline in mean abdominal pain, at least 3 CSBMs and an increase of at least 1 CSBM from baseline, all in the same week, for at least 9 out of the first 12 weeks of treatment. Each of the 2 components of the 9 out of 12 weeks combined responder endpoint, abdominal pain and CSBMs, was also a primary endpoint.

For the 6 out of 12 weeks combined primary responder endpoint, a patient had to have at least a 30% reduction from baseline in mean abdominal pain and an increase of at least 1 CSBM from baseline, all in the same week, for at least 6 out of the first 12 weeks of treatment. To be considered a responder for this analysis, patients did not have to have at least 3 CSBMs per week.

The efficacy results for the 9 out of 12 weeks and the 6 out of 12 weeks responder endpoints are shown in Tables 3 and 4, respectively. In both trials, the proportion of patients who were responders to LINZESS 290 mcg was statistically significantly higher than with placebo.

Table 3: Efficacy Responder Rates in Two Placebo-Controlled Trials of Adults with IBS-C (Trials 1 and 2): At Least 9 Out of 12 Weeks
 | Trial 1 |  |  | Trial 2
 | LINZESS 290 mcg Once Daily (N=405) | Placebo (N=395) | Treatment Difference [95% CI] | LINZESS 290 mcg Once Daily (N=401) | Placebo (N=403) | Treatment Difference [95% CI]
Combined Responder* (Abdominal Pain and CSBM Responder) | 12% | 5% | 7% [3.2%, 10.9%] | 13% | 3% | 10% [6.1%, 13.4%]
Abdominal Pain Responder* (≥ 30% Abdominal Pain Reduction) | 34% | 27% | 7% [0.9%, 13.6%] | 39% | 20% | 19% [13.2%, 25.4%]
CSBM Responder* (≥ 3 CSBMs and Increase ≥1 CSBM from Baseline) | 20% | 6% | 13% [8.6%, 17.7%] | 18% | 5% | 13% [8.7%, 17.3%]
* Primary Endpoints
Note: Analyses based on first 12 weeks of treatment for both Trials 1 and 2
CI =Confidence Interval

Table 4: Efficacy Responder Rates in Two Placebo-Controlled Trials of Adults with IBS-C (Trials 1 and 2): At Least 6 Out of 12 Weeks
 | Trial 1 |  |  | Trial 2
 | LINZESS 290 mcg Once Daily (N=405) | Placebo (N=395) | Treatment Difference [95% CI] | LINZESS 290 mcg Once Daily (N=401) | Placebo (N=403) | Treatment Difference [95% CI]
Combined Responder* (Abdominal Pain and CSBM Responder) | 34% | 21% | 13% [6.5%, 18.7%] | 34% | 14% | 20% [14.0%, 25.5%]
Abdominal Pain Responder** (≥ 30% Abdominal Pain Reduction) | 50% | 37% | 13% [5.8%, 19.5%] | 49% | 34% | 14% [7.6%, 21.1%]
CSBM Responder** (Increase ≥ 1 CSBM from Baseline) | 49% | 30% | 19% [12.4%, 25.7%] | 48% | 23% | 25% [18.7%, 31.4%]
* Primary Endpoint, ** Secondary Endpoints
Note: Analyses based on first 12 weeks of treatment for both Trials 1 and 2
CI =Confidence Interval

In each trial, improvement from baseline in abdominal pain and CSBM frequency was seen over the first 12-weeks of the treatment periods. For change from baseline in the 11-point abdominal pain scale, LINZESS 290 mcg began to separate from placebo in the first week. Maximum effects were seen at weeks 6 - 9 and were maintained until the end of the study. The mean treatment difference from placebo at week 12 was a decrease in pain score of approximately 1.0 point in both trials (using an 11-point scale). Maximum effect on CSBM frequency occurred within the first week, and for change from baseline in CSBM frequency at week 12, the difference between placebo and LINZESS was approximately 1.5 CSBMs per week in both trials.

In each trial, in addition to improvements in abdominal pain and CSBM frequency over the first 12 weeks of the treatment period, improvements were observed in the following when LINZESS was compared to placebo: SBM frequency [SBMs/week], stool consistency [as measured by the Bristol Stool Form Scale (BSFS)], and amount of straining with bowel movements [amount of time pushing or physical effort to pass stool].

During the 4-week randomized withdrawal period in Trial 1, patients who received LINZESS during the 12-week treatment period were re-randomized to receive placebo or continue treatment on LINZESS 290 mcg. In LINZESS-treated patients re-randomized to placebo, CSBM frequency and abdominal-pain severity returned toward baseline within 1 week and did not result in worsening compared to baseline. Patients who continued on LINZESS maintained their response to therapy over the additional 4 weeks. Patients on placebo who were allocated to LINZESS had an increase in CSBM frequency and a decrease in abdominal pain levels that were similar to the levels observed in patients taking LINZESS during the treatment period.

Trial 6 (NCT03573908) was a randomized, double-blind, placebo-controlled, parallel-group trial that evaluated the safety and efficacy of LINZESS in patients with IBS-C over a 12-week treatment period followed by a 4-week randomized withdrawal period. A total of 614 patients [mean age of 47 years (range 18 to 85 years), 81% female, 63% white, 24% black, and 27% Hispanic] received treatment with LINZESS 290 mcg or placebo once daily and all patients met Rome III criteria for IBS-C.

The efficacy of LINZESS was assessed using a primary endpoint based on the mean abdominal score (composite of abdominal bloating, abdominal discomfort, and abdominal pain) across 12 weeks. The secondary endpoint was a responder analysis based on at least a 2.5-point improvement in the abdominal score from baseline for at least 6 out of 12 weeks as shown in Table 5.

Table 5: Efficacy Endpoints in a Placebo-Controlled Trial of Adults with IBS-C (Trial 6): Overall Change from Baseline in Abdominal Score and Responder Rates for at Least 6 Out of 12 Weeks
 | Trial 6
 | LINZESS 290 mcg Once Daily (N=306) | Placebo (N=308) | Treatment Difference [95% CI]
Baseline Abdominal Score | 6.4 | 6.5
Least Squares 12-week Mean Change from Baseline in Abdominal Score* | -1.9 | -1.2 | -0.7 [-1.0, -0.4]
Abdominal Score 6 of 12-Week Responder** | 34% | 18.5% | 15.5% [8.6%, 22.3%]
* Primary Endpoint, ** Secondary Endpoint
Each abdominal symptom was rated on a 0-to-10-point numeric rating scale where 0=no [symptom] and 10=worst possible [symptom].
CI = Confidence Interval

14.2 Irritable Bowel Syndrome with Constipation (IBS-C) in Pediatric Patients 7 Years of Age and Older

The efficacy of LINZESS for the treatment of IBS-C in pediatric patients 7 to 17 years of age was established in a 12-week double-blind, parallel-group, randomized, multicenter, clinical trial (Trial 8; NCT04026113). A total of 108 patients were randomized to receive treatment with LINZESS 145 mcg once daily or a higher than recommended dosage of LINZESS. The higher LINZESS dosage group did not demonstrate additional treatment benefit compared to LINZESS 145 mcg once daily. A total of 53 patients who received LINZESS 145 mcg once daily were evaluated for efficacy. The evaluated patients had a mean age of 13 years (range 7 to 17 years); 57% were female; 34% identified as Hispanic or Latino; 72% identified as White, 25% as Black or African American, and 4% as Asian.

All patients met Rome III criteria for child/adolescent IBS-C requiring that, for at least once per week for at least 2 months before the screening visit, the participant experienced abdominal discomfort (an uncomfortable sensation not described as pain) or pain associated with 2 or more of the following at least 25% of the time:

- Improvement with defecation

- Onset associated with a change in frequency of stool
- Onset associated with a change in form (appearance) of stool

Patients were also required to have an average daytime abdominal pain score of ≥1 (on a 0-4 scale) and had an average of fewer than 3 SBMs per week during the 14 days before randomization.

The primary endpoint was the proportion of patients who achieved at least a 30% reduction in abdominal pain and an increase of at least 2 spontaneous bowel movements (SBMs)/week from baseline for at least 6 out of 12 weeks (combined responder). The result of the primary efficacy endpoint is shown in Table 6.

Table 6: Efficacy Responder Rate in Pediatric Patients 7 to 17 Years of Age with IBS-C (Trial 8): At Least 6 out of 12 Weeks
 | Trial 8
 | LINZESS 145 mcg Once Daily n (%) [95% CI] N=53
Combined Responder† (Abdominal Pain and SBM Responder) | 16 (30%) [18%, 44%]
Abdominal Pain Responder (≥ 30% Abdominal Pain Reduction) | 36 (68%)
SBM Responder (Increase ≥ 2 SBMs from Baseline) | 21 (40%)
† The primary endpoint of combined responder is defined as a patient who has at least a 30% reduction in abdominal pain and an increase of at least 2 SBMs/week from baseline for at least 6 out of 12 weeks.

Abdominal pain and SBM frequency improved during week 1 and improvement was maintained throughout the remainder of the 12-week treatment period.

14.3 Chronic Idiopathic Constipation (CIC) in Adults

The efficacy of LINZESS for the treatment of CIC was established in two double-blind, placebo-controlled, randomized, multicenter clinical trials in adult patients (Trials 3 and 4). A total of 642 patients in Trial 3 and 630 patients in Trial 4 [overall mean age of 48 years (range 18 to 85 years), 89% female, 76% white, 22% black, 10% Hispanic] received treatment with LINZESS 145 mcg, 290 mcg, or placebo once daily and were evaluated for efficacy. All patients met modified Rome II criteria for functional constipation. Modified Rome II criteria were less than 3 Spontaneous Bowel Movements (SBMs) per week and 1 of the following symptoms for at least 12 weeks, which need not be consecutive, in the preceding 12 months:

- Straining during greater than 25% of bowel movements
- Lumpy or hard stools during greater than 25% of bowel movements
- Sensation of incomplete evacuation during greater than 25% of bowel movements

Patients were also required to have less than 3 CSBMs per week and less than or equal to 6 SBMs per week during a 2-week baseline period. Patients were excluded if they met criteria for IBS-C or had fecal impaction that required emergency room treatment.

The trial designs were identical through the first 12 weeks. Trial 3 also included an additional 4-week randomized withdrawal (RW) period. During the trials, patients were allowed to continue stable doses of bulk laxatives or stool softeners but were not allowed to take laxatives, bismuth, prokinetic agents, or other drugs to treat chronic constipation.

The efficacy of LINZESS was assessed using a responder analysis and change-from-baseline endpoints. Results for endpoints were based on information provided daily by patients in diaries.

A CSBM responder in the CIC trials was defined as a patient who had at least 3 CSBMs and an increase of at least 1 CSBM from baseline in a given week for at least 9 weeks out of the 12-week treatment period. The CSBM responder rates are shown in Table 6. During the individual double-blind placebo-controlled trials, LINZESS 290 mcg did not consistently offer additional clinically meaningful treatment benefit over placebo than that observed with the LINZESS 145 mcg dose. Therefore, the 145 mcg dose is the recommended dose. Only the data for the approved 145 mcg dose of LINZESS are presented in Table 7.

In Trials 3 and 4, the proportion of patients who were CSBM responders was statistically significantly greater with the LINZESS 145 mcg dose than with placebo.

Table 7: Efficacy Responder Rates in Two Placebo-Controlled Trials of Adults with CIC (Trials 3 and 4): At Least 9 Out of 12 Weeks
 | Trial 3 |  |  | Trial 4
 | LINZESS 145 mcg Once Daily (N=217) | Placebo (N=209) | Treatment Difference [95% CI] | LINZESS 145 mcg Once Daily (N=213) | Placebo (N=215) | Treatment Difference [95% CI]
CSBM Responder* (≥ 3 CSBMs and Increase ≥ 1 CSBM from Baseline) | 20% | 3% | 17% [11.0%, 22.8%] | 15% | 6% | 10% [4.2%, 15.7%]
*Primary Endpoint
CI=Confidence Interval

CSBM frequency reached maximum level during week 1 and was also demonstrated over the remainder of the 12-week treatment period in Trial 3 and Trial 4. For the mean change from baseline in CSBM frequency at week 12, the difference between placebo and LINZESS was approximately 1.5 CSBMs.

On average, patients who received LINZESS across the 2 trials had significantly greater improvements compared with patients receiving placebo in stool frequency (CSBMs/week and SBMs/week), and stool consistency (as measured by the BSFS).

In each trial, in addition to improvements in CSBM frequency over the first 12 weeks of the treatment period, improvements were observed in each of the following when LINZESS was compared to placebo: SBM frequency [SBMs/week], stool consistency [as measured by the BSFS], and amount of straining with bowel movements [amount of time pushing or physical effort to pass stool].

During the 4-week randomized withdrawal period in Trial 3, patients who received LINZESS during the 12-week treatment period were re-randomized to receive placebo or continue treatment on the same dose of LINZESS taken during the treatment period. In LINZESS-treated patients re-randomized to placebo, CSBM and SBM frequency returned toward baseline within 1 week and did not result in worsening compared to baseline. Patients who continued on LINZESS maintained their response to therapy over the additional 4 weeks. Patients on placebo who were allocated to LINZESS had an increase in CSBM and SBM frequency similar to the levels observed in patients taking LINZESS during the treatment period.

A 72 mcg dose of LINZESS was established in a randomized, double-blind, placebo-controlled, multicenter clinical trial in adult patients (Trial 5). A total of 1223 patients [overall mean age of 46 years (range 18 to 90 years), 77% female, 71% white, 24% black, 43% Hispanic] received treatment with LINZESS 72 mcg or placebo once daily and were evaluated for efficacy. All patients met modified Rome III criteria for functional constipation. Trial 5 was identical to Trials 3 and 4 through the first 12 weeks. The efficacy of the 72 mcg dose was assessed using a responder analysis where a CSBM responder was defined as a patient who had at least 3 CSBMs and an increase of at least 1 CSBM from baseline in a given week for at least 9 weeks out of the 12-week treatment period, which was the same as the one defined in Trials 3 and 4. The response rates for the CSBM responder endpoint were 13% for LINZESS 72 mcg and 5% for placebo. The difference between LINZESS 72 mcg and placebo was 9% (95% CI: 4.8%, 12.5%).

A separate analysis was performed using an alternate CSBM responder definition. In this analysis a CSBM responder was defined as a patient who had at least 3 CSBMs and an increase of at least 1 CSBM from baseline in a given week for at least 9 weeks out of the 12-week treatment period and at least 3 of the last 4 weeks of the treatment period. The response rates for the alternate CSBM responder endpoint were 12% for LINZESS 72 mcg and 5% for placebo. The difference between LINZESS 72 mcg and placebo was 8% (95% CI: 3.9%, 11.5%).

14.4 Functional Constipation (FC) in Pediatric Patients 6 Years of Age and Older

The efficacy of LINZESS for the treatment of FC in pediatric patients 6 to 17 years of age was established in a 12-week double-blind, placebo-controlled, randomized, multicenter, clinical trial (Trial 7; NCT04026113). A total of 328 patients received treatment with LINZESS 72 mcg or placebo once daily and were evaluated for efficacy. Patients in the trial had a mean age of 11 years (range 6 to 17 years); 55% were female; 45% identified as Hispanic or Latino; 70% identified as White, 26% as Black or African American, 2% as Asian, and 2% identified as another racial group. For trial enrollment, Rome III criteria for child/adolescent FC were modified to require that patients have less than 3 Spontaneous Bowel Movements (SBMs) per week (defined as a BM that occurred in the absence of laxative, enema, or suppository use on the calendar day of or before the BM) and 1 or more of the following criteria at least once per week for at least 2 months before the screening visit:

- History of stool withholding or excessive voluntary stool retention
- History of painful or hard bowel movements (BMs)
- History of large diameter stools that may obstruct the toilet
- Presence of a large fecal mass in the rectum
- At least 1 episode of fecal incontinence per week

Patients were also required to have an average of less than 3 SBMs per week during the 2-week baseline period. Patients were excluded if they met criteria for pediatric IBS-C or had fecal impaction. Patients were allowed to continue previously stable doses of bulk laxatives, fiber, stool softeners, or probiotics. During the trial, patients could use bisacodyl or senna as needed, but were not allowed to take other laxatives, bismuth, prokinetic agents, or other drugs to treat functional constipation.

The efficacy of LINZESS in the treatment of FC in pediatric patients 6 to 17 years of age was assessed using change-from-baseline endpoints. The primary efficacy endpoint was the 12-week change from baseline in SBM frequency rate. The results demonstrated that patients who received LINZESS had statistically significant improvements compared with placebo as shown in Table 8.

Table 8: Efficacy Endpoint in Placebo-Controlled Trial of Pediatric Patients 6 to 17 Years of Age with FC (Trial 7): 12-week Change from Baseline in SBM Frequency Rate (SBMs/week)
 | Trial 7
 | LINZESS 72 mcg Once Daily (N=164) | Placebo (N=164) | Treatment Difference [95% CI]
Baseline SBM Frequency Rate | 1.2 | 1.3
Least Squares 12-week Mean Change from Baseline in SBM Frequency Rate* | 2.6 | 1.3 | 1.3 [0.7, 1.8]
* Primary Endpoint
CI = Confidence Interval

SBM frequency improved during week 1 and was maintained throughout the remainder of the 12-week treatment period.

16 HOW SUPPLIED/STORAGE AND HANDLING

How Supplied

LINZESS Capsule Strength | Description | Packaging | NDC number
72 mcg | White to off-white opaque hard gelatin capsules with gray imprint “FL 72” | Bottle of 30 | 0456-1203-30
145 mcg | White to off-white opaque hard gelatin capsules with gray imprint "FL 145" | Bottle of 30 | 0456-1201-30
290 mcg | White to off-white opaque hard gelatin capsules with gray imprint "FL 290" | Bottle of 30 | 0456-1202-30

Storage

Store at 25°C (77°F); excursions permitted between 15°C and 30°C (59°F and 86°F) [see USP Controlled Room Temperature].

Keep LINZESS in the original container. Do not subdivide or repackage. Protect from moisture. Do not remove desiccant from the container. Keep bottles tightly closed in a dry place.

17 PATIENT COUNSELING INFORMATION

Advise the patient to read the FDA-approved patient labeling (Medication Guide).

Advise patients:

Diarrhea

- To stop LINZESS and contact their healthcare provider if they experience unusual or severe abdominal pain, and/or severe diarrhea, especially if in combination with hematochezia or melena [see Warnings and Precautions (5.2)].

Accidental Ingestion

- Accidental ingestion of LINZESS in children especially in patients less than 2 years of age may result in severe diarrhea and dehydration. Instruct patients to take steps to store LINZESS securely and out of reach of children, and to dispose of unused LINZESS [see Contraindications (4), Warnings and Precautions (5.1, 5.2)].

Administration and Handling Instructions

- To take LINZESS once daily on an empty stomach at least 30 minutes prior to a meal at approximately the same time each day [see Dosage and Administration (2.2)].
- If a dose is missed, skip the missed dose and take the next dose at the regular time. Do not take 2 doses at the same time.
- To swallow LINZESS capsules whole. Do not crush or chew capsules or capsule contents.
- For patients who are unable to swallow the capsule whole, LINZESS capsules can be opened and administered orally in either applesauce or with bottled water or administered with water via a nasogastric or gastrostomy tube, as described in the Medication Guide.
- To keep LINZESS in the original container. Do not subdivide or repackage. Protect from moisture. Do not remove desiccant from the container. Keep bottles closed tightly in a dry place.

Marketed by:

AbbVie, Inc.
North Chicago, IL 60064

Ironwood Pharmaceuticals, Inc.
Boston, MA, 02110

© 2025 AbbVie and Ironwood Pharmaceuticals, Inc. All rights reserved.
LINZESS and its design are registered trademarks of Ironwood Pharmaceuticals, Inc.

For more information, go to www.LINZESS.com or call 1-800-678-1605.
20096895

MEDICATION GUIDE
LINZESS® (lin-ZESS)
(linaclotide)
capsules, for oral use

What is the most important information I should know about LINZESS?

- Do not give LINZESS to children who are less than 2 years of age. It may harm them.

See the section “What are the possible side effects of LINZESS?” for more information about side effects.

What is LINZESS?
LINZESS is a prescription medicine used to treat:

- irritable bowel syndrome with constipation (IBS-C) in adults and in children and adolescents 7 years of age and older.
- a type of constipation called chronic idiopathic constipation (CIC) in adults. “Idiopathic” means the cause of the constipation is unknown.
- functional constipation in children and adolescents 6 years of age and older.

It is not known if LINZESS is safe and effective in children with functional constipation less than 6 years of age or in children with IBS-C less than 7 years of age.

Who should not take LINZESS?

- Do not give LINZESS to children who are less than 2 years of age. LINZESS can cause severe diarrhea and your child could get severe dehydration (loss of a large amount of body water and salt).
- Do not take LINZESS if a healthcare provider has told you that you have a bowel blockage (intestinal obstruction).

Before you take LINZESS, tell your healthcare provider about all of your medical conditions, including if you:

- are pregnant or plan to become pregnant. It is not known if LINZESS will harm your unborn baby.
- are breastfeeding or plan to breastfeed. You and your healthcare provider should decide if you will take LINZESS and breastfeed.

Tell your healthcare provider about all the medicines you take, including prescription and over-the-counter medicines, vitamins and herbal supplements.

How should I take LINZESS?

- Take LINZESS exactly as your healthcare provider tells you to take it.
- Take LINZESS 1 time each day on an empty stomach, at least 30 minutes before a meal, at approximately the same time each day. You should also wait 30 minutes before eating a meal if you take LINZESS with applesauce or mixed with water.
- If you miss a dose, skip the missed dose. Just take the next dose at your regular time. Do not take 2 doses at the same time.
- LINZESS capsules should be swallowed whole. Do not crush or chew LINZESS.
  - If you cannot swallow LINZESS capsules whole, you may open the LINZESS capsule and sprinkle the LINZESS beads over applesauce or mix LINZESS with bottled water before swallowing.

It is not known if LINZESS is safe and effective when sprinkled on other foods or mixed with other liquids.
Taking LINZESS in applesauce:

- Place 1 teaspoon of room temperature applesauce into a clean container. Open the LINZESS capsule and sprinkle all of the LINZESS beads onto the applesauce.
- Swallow all of the LINZESS beads and applesauce right away. Do not keep the applesauce for later use.
- Do not chew the LINZESS beads.

Taking LINZESS in water:

- Pour 1 ounce (30 mL) of room temperature bottled water into a clean cup. Open the LINZESS capsule and sprinkle all of the LINZESS beads into the cup of water.
- Gently swirl the beads and water for at least 20 seconds.
- Swallow all of the LINZESS beads and water mixture right away. Do not keep the mixture for later use.
- If you see any LINZESS beads left in the cup, add another 1 ounce (30 mL) of water to the beads in the cup, swirl for at least 20 seconds, and swallow right away.

Taking LINZESS in a nasogastric or gastrostomy feeding tube:
Gather the supplies you will need to take your LINZESS dose. Your healthcare provider should tell you what size catheter tipped syringe you will need for your dose. Ask your healthcare provider if you have any questions about how to give LINZESS the right way.

- Open the LINZESS capsule and pour all of the LINZESS beads into a clean container with 1 ounce (30 mL) of room temperature bottled water.
- Gently swirl the beads and water for at least 20 seconds.
- Remove the plunger from the catheter tipped syringe, and then pour the LINZESS bead and water mixture into the syringe and replace the plunger.
- Remove the cap from the syringe, insert the tip of the syringe into the nasogastric or gastrostomy feeding tube and push the plunger all the way in to give the dose.
- If you see any LINZESS beads left in the container, add another 1 ounce (30 mL) of water to the beads in the container and repeat the process.
- After giving the LINZESS dose, flush the nasogastric or gastrostomy feeding tube with at least 10 mL of water.

What are the possible side effects of LINZESS?
LINZESS can cause serious side effects, including:

- See “What is the most important information I should know about LINZESS?”
- Diarrhea is the most common side effect of LINZESS, and it can sometimes be severe.
  ◦ Diarrhea often begins within the first 2 weeks of LINZESS treatment.
  ◦ Stop taking LINZESS and call your healthcare provider right away if you get severe diarrhea during treatment with LINZESS.

Other common side effects of LINZESS in people with IBS-C and CIC include:

- gas
- stomach-area (abdomen) pain
- swelling, or a feeling of fullness or pressure in your abdomen (distention)

Call your healthcare provider or go to the nearest hospital emergency room right away, if you develop unusual or severe stomach-area (abdomen) pain, especially if you also have bright red, bloody stools or black stools that look like tar.
These are not all the possible side effects of LINZESS.
Call your doctor for medical advice about side effects. You may report side effects to FDA at 1-800-FDA-1088.

How should I store LINZESS?

- Store LINZESS at room temperature between 68°F to 77°F (20°C to 25°C).
- Keep LINZESS in the bottle that it comes in.
- The LINZESS bottle contains a desiccant packet to help keep your medicine dry (protect it from moisture). Do not remove the desiccant packet from the bottle.
- Keep the bottle of LINZESS tightly closed and in a dry place.

Keep LINZESS and all medicines out of the reach of children.

General information about the safe and effective use of LINZESS.
Medicines are sometimes prescribed for purposes other than those listed in a Medication Guide. Do not use LINZESS for a condition for which it was not prescribed. Do not give LINZESS to other people, even if they have the same symptoms that you have. It may harm them.
You can ask your healthcare provider or pharmacist for information about LINZESS that is written for health professionals.

What are the ingredients in LINZESS?
Active ingredient: linaclotide
Inactive ingredients for the 145 mcg and 290 mcg capsules: calcium chloride dihydrate, hypromellose, L-leucine, and microcrystalline cellulose. Capsule shell: gelatin and titanium dioxide.
Inactive ingredients for the 72 mcg capsules: calcium chloride dihydrate, L-histidine, microcrystalline cellulose, polyvinyl alcohol, and talc. Capsule shell: gelatin and titanium dioxide.
LINZESS® is a registered trademark of Ironwood Pharmaceuticals, Inc.
Marketed by: AbbVie, Inc. North Chicago, IL 60064 and Ironwood Pharmaceuticals, Inc. Boston, MA 02110
© 2025 AbbVie and Ironwood Pharmaceuticals, Inc. All rights reserved.
For more information, go to www.LINZESS.com or call 1-800-678-1605.

This Medication Guide has been approved by the U.S. Food and Drug Administration Revised:11/2025

20092576

PRINCIPAL DISPLAY PANEL

NDC 0456-1203-30
Rx Only
30 CAPSULES
Linzess
(linaclotide) capsules
72 mcg/capsule

PRINCIPAL DISPLAY PANEL

NDC 0456-1201-30
Rx Only
30 CAPSULES
Linzess
(linaclotide) capsules
145 mcg/capsule

PRINCIPAL DISPLAY PANEL

NDC 0456-1202-30
Rx Only
30 CAPSULES
Linzess
(linaclotide) capsules
290 mcg/capsule